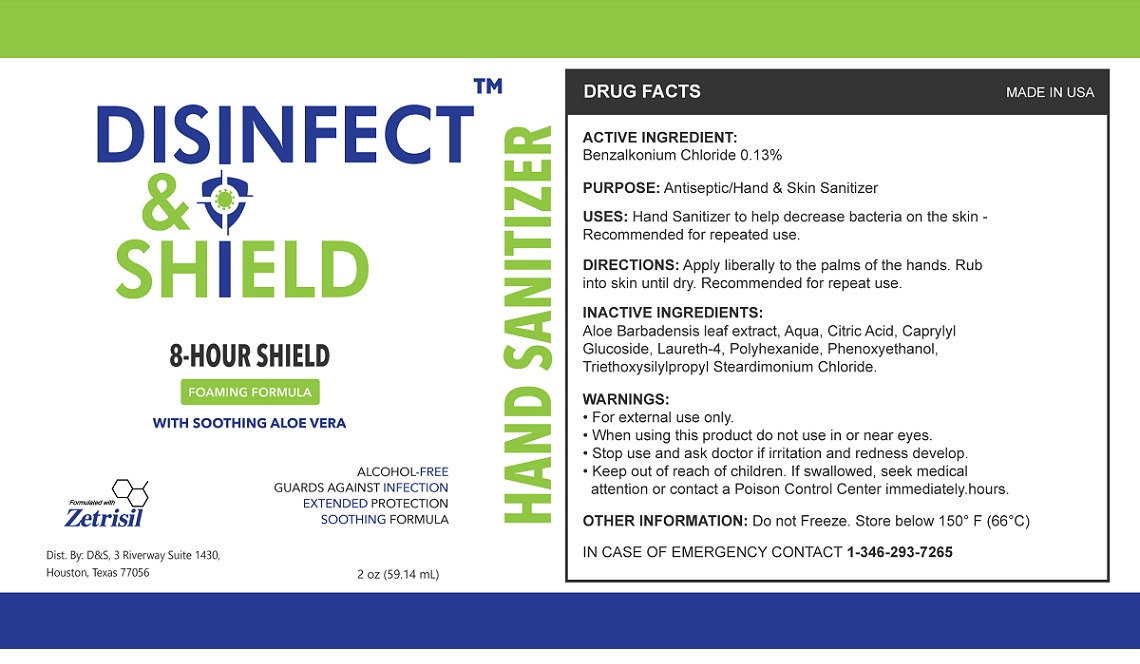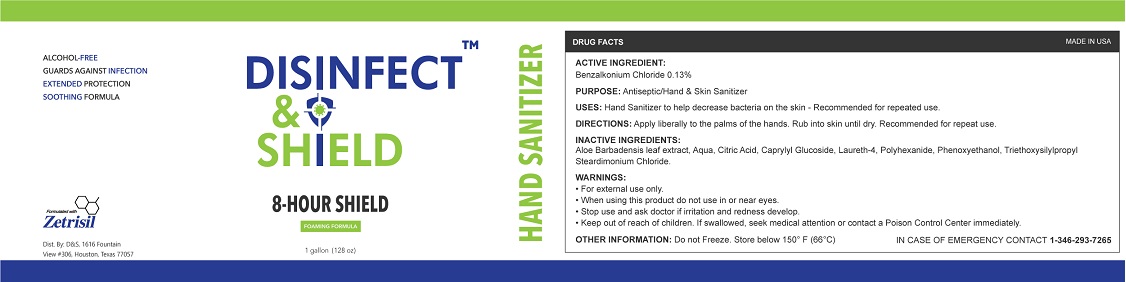 DRUG LABEL: Disinfect and Shield Hand Sanitizer Foam
NDC: 71884-022 | Form: LIQUID
Manufacturer: Enviro Specialty Chemicals Inc
Category: otc | Type: HUMAN OTC DRUG LABEL
Date: 20200810

ACTIVE INGREDIENTS: BENZALKONIUM CHLORIDE 0.13 g/100 mL
INACTIVE INGREDIENTS: ALOE VERA LEAF; WATER; CITRIC ACID MONOHYDRATE; CAPRYLYL GLUCOSIDE; LAURETH-4; POLIHEXANIDE; PHENOXYETHANOL; TRIETHOXYSILYLPROPYL STEARDIMONIUM CHLORIDE

DISINFECT™ & SHIELD HAND SANITIZER

ACTIVE INGREDIENT:

Benzalkonium Chloride 0.13%

PURPOSE: Antiseptic/Hand & Skin Sanitizer

INDICATIONS AND USAGE

USES: Hand Sanitizer to help decrease bacteria on the skin - Recommended for repeated use.

DOSAGE AND ADMINISTRATION

DIRECTIONS: Apply liberally to the palms of the hands. Rub into skin until dry. Recommended for repeat use.

OTHER INFORMATION: Do not Freeze. Store below 150° F (66°C)

INACTIVE INGREDIENTS:

Aloe Barbadensis leaf extract, Aqua, Citric Acid, Caprylyl Glucoside, Laureth-4, Polyhexanide, Phenoxyethanol, Triethoxysilylpropyl Steardimonium Chloride.

WARNINGS:

• For external use only.

• When using this product do not use in or near eyes.

• Stop use and ask a doctor if irritation and redness develop.

• Keep out of reach of children. If swallowed, seek medical attention or contact a Poison Control Center immediately hours.

QUESTIONS

IN CASE OF EMERGENCY CONTACT 1-346-293-7265

8-HOUR SHIELD

FOAMING FORMULA

WITH SOOTHING ALOE VERA

ALCOHOL-FREE

GUARDS AGAINST INFECTION

EXTENDED PROTECTION

SOOTHING FORMULA

Formulated with

Zetrisil

Dist. By: D&S, 3 Riverway Suite 1430,

Houston, Texas 77056

MADE IN USA